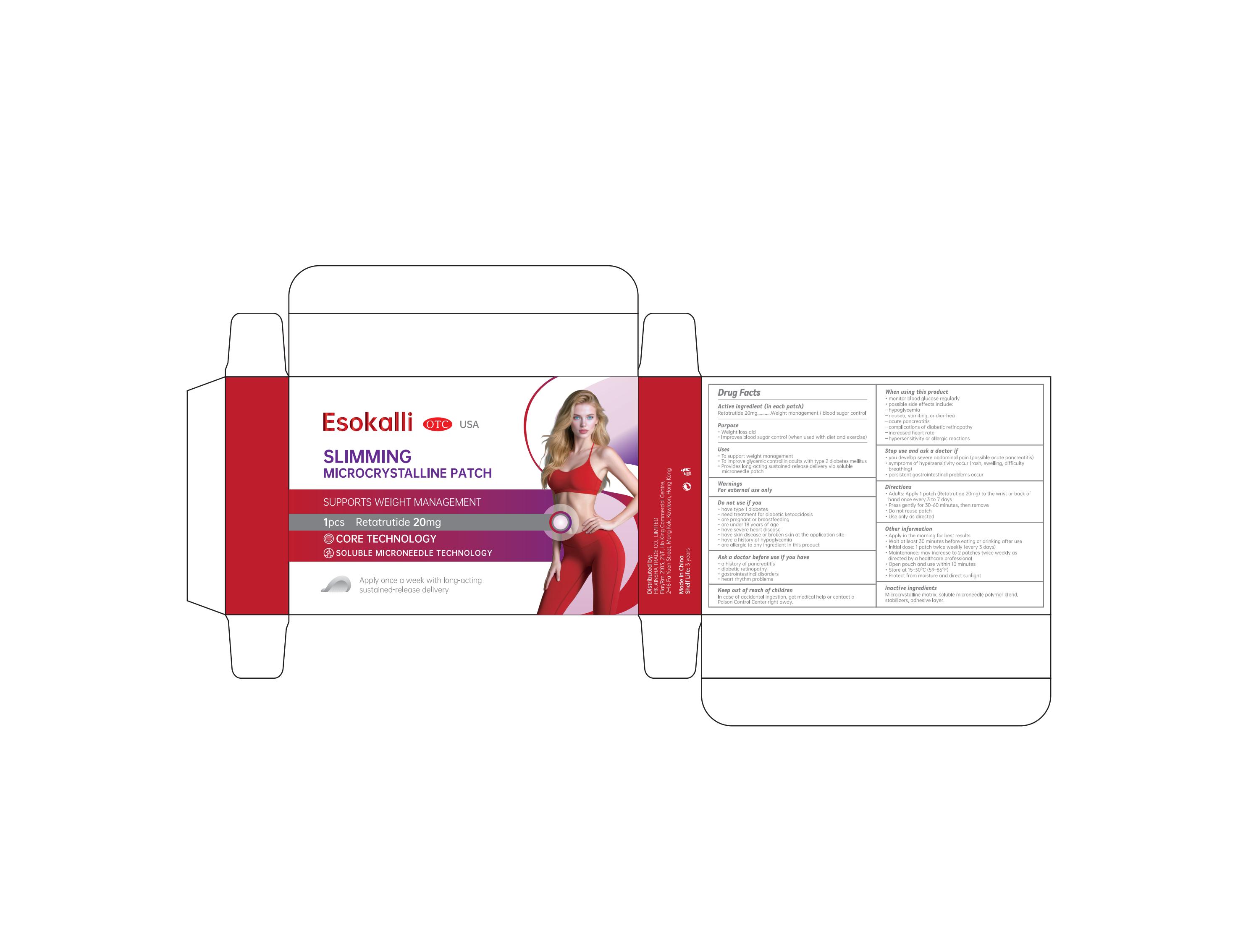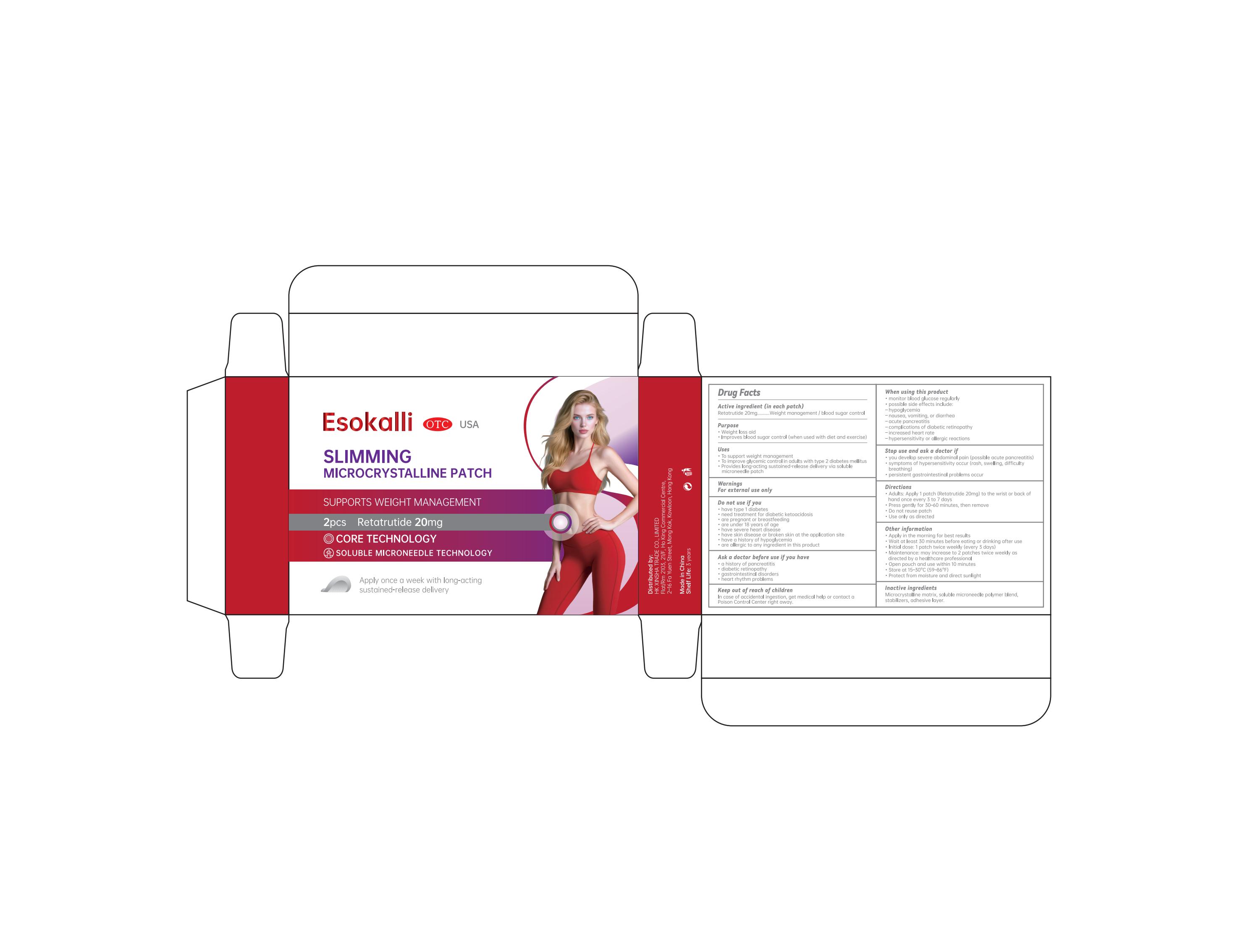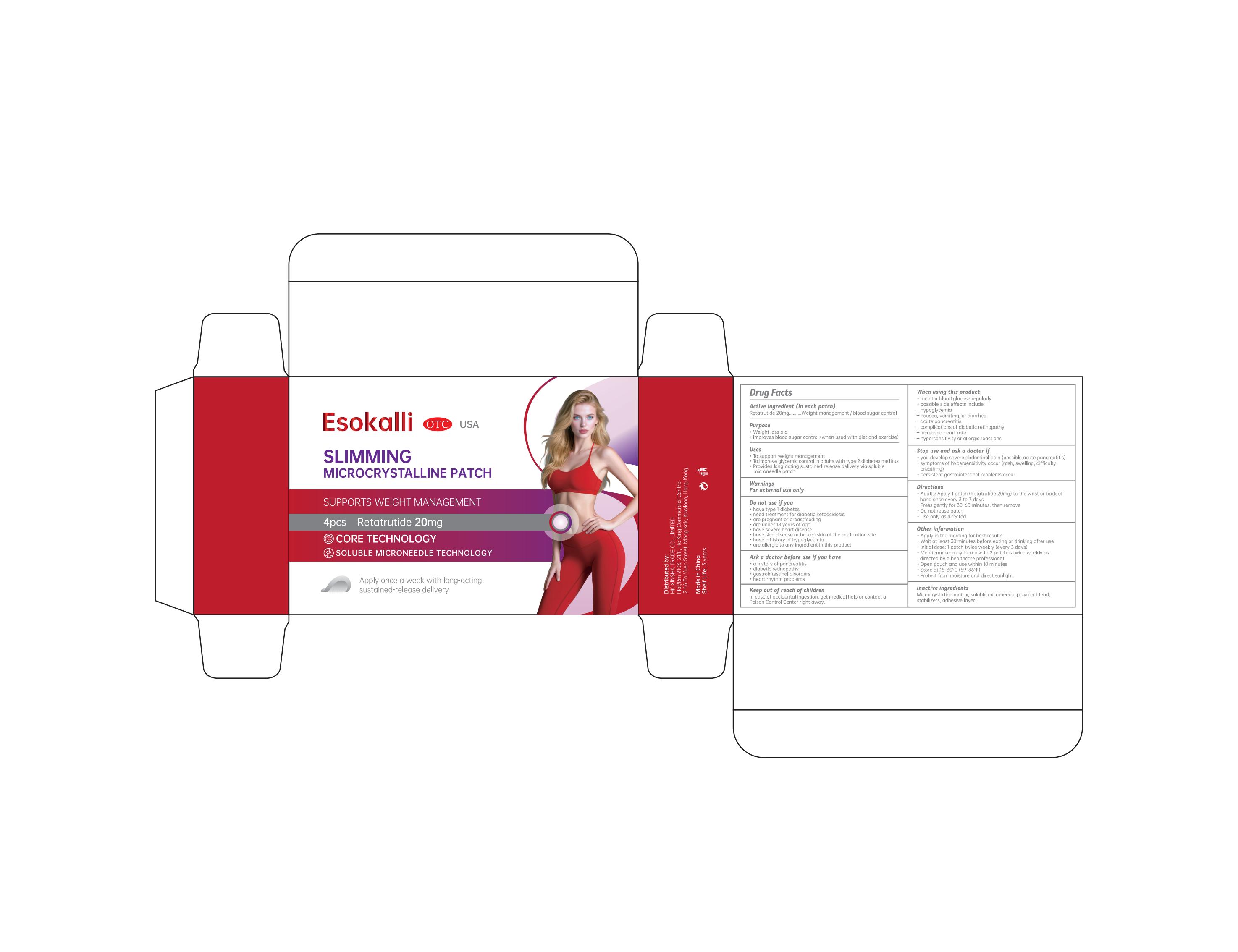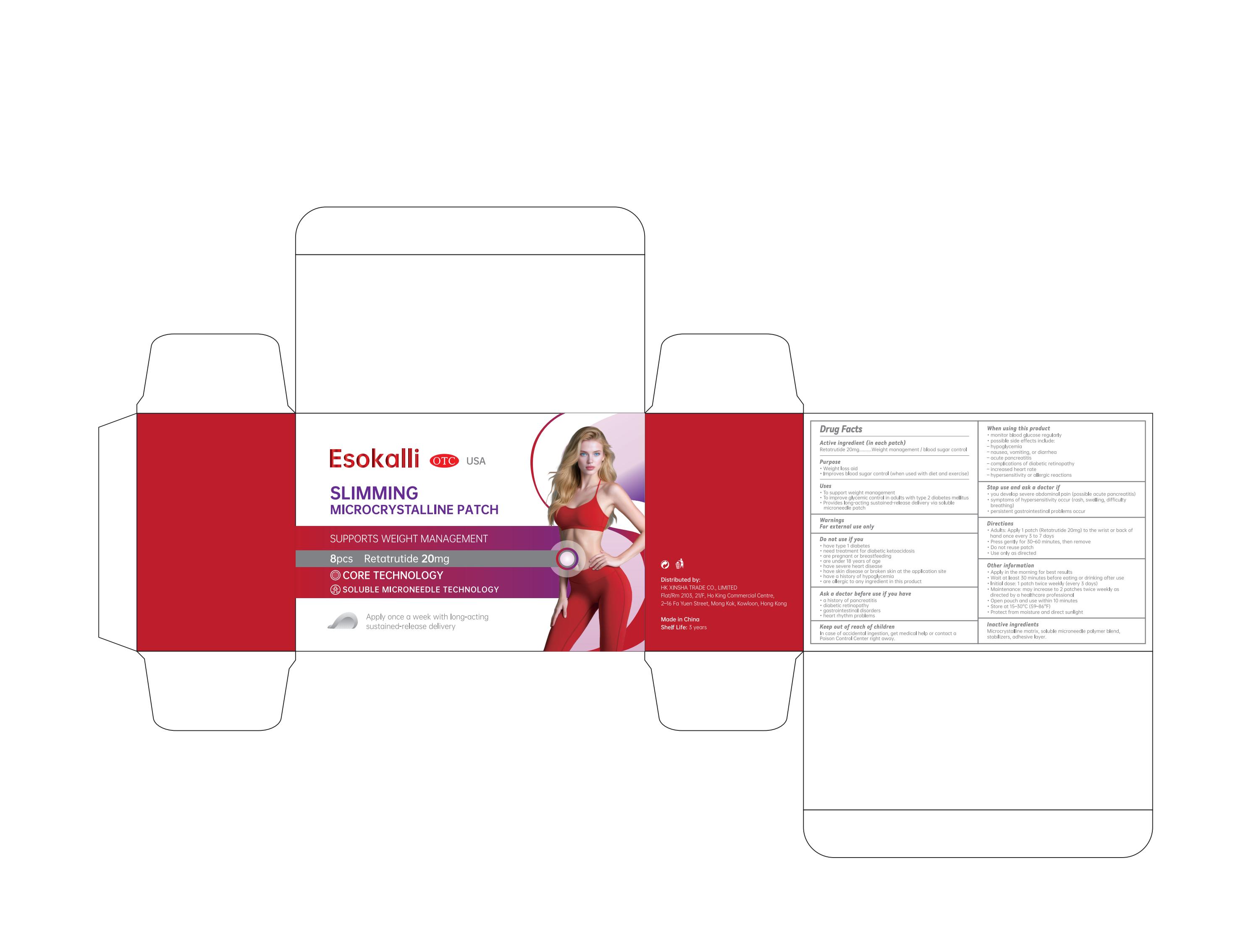 DRUG LABEL: Esokalli Slimming microcrystalline patch
NDC: 84778-078 | Form: PATCH
Manufacturer: Guangzhou Yixin Cross-border E-commerce Co., Ltd.
Category: otc | Type: HUMAN OTC DRUG LABEL
Date: 20250824

ACTIVE INGREDIENTS: RETATRUTIDE 20 U/100 U
INACTIVE INGREDIENTS: CELLULOSE, MICROCRYSTALLINE; POLYVINYL ALCOHOL, UNSPECIFIED; DIMETHICONE, UNSPECIFIED; SUCROSE

Active ingredient (in each patch)

Retatrutide 1.6 mg ……………………………. Weight management / blood sugar control

Purpose

Weight loss aid
Improves blood sugar control (when used with diet and exercise)

Uses

To support weight management
To improve glycemic control in adults with type 2 diabetes mellitus
Provides long-acting sustained-release delivery via soluble microneedle patch

Warnings

For external use only

Dosage and administration

For external use only.

Do not use if you

have type 1 diabetes
need treatment for diabetic ketoacidosis
are pregnant or breastfeeding
are under 18 years of age

When using this product

monitor blood glucose regularly

possible side effects include:
hypoglycemia

nausea, vomiting, or diarrhea

acute pancreatitis

complications of diabetic retinopathy

increased heart rate

hypersensitivity or allergic reactions

Stop use and ask a doctor if

• you develop severe abdominal pain (possible acute pancreatitis)

• symptoms of hypersensitivity occur (rash, swelling, difficulty breathing)

• persistent gastrointestinal problems occur

Keep out of reach of children.

In case of accidental ingestion, get medical help or contact a Poison Control Center right away.

Inactive ingredients

Microcrystalline matrix, soluble microneedle polymer blend, stabilizers, adhesive layer.